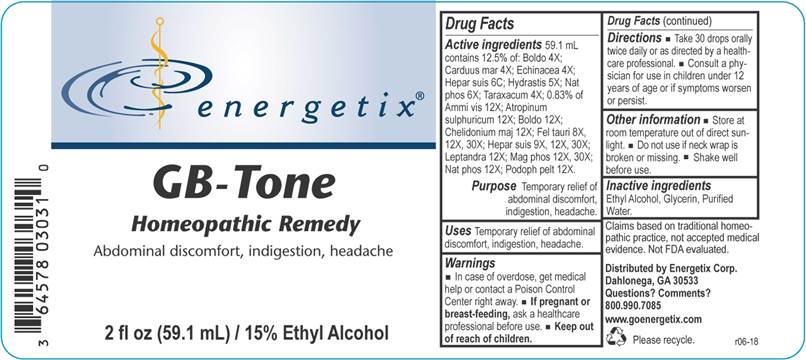 DRUG LABEL: GB-Tone
NDC: 64578-0130 | Form: LIQUID
Manufacturer: Energetix Corp
Category: homeopathic | Type: HUMAN OTC DRUG LABEL
Date: 20180711

ACTIVE INGREDIENTS: AMMI VISNAGA FRUIT 12 [hp_X]/1 mL; ATROPINE SULFATE 12 [hp_X]/1 mL; PEUMUS BOLDUS LEAF 4 [hp_X]/1 mL; MILK THISTLE 4 [hp_X]/1 mL; CHELIDONIUM MAJUS 12 [hp_X]/1 mL; ECHINACEA ANGUSTIFOLIA 4 [hp_X]/1 mL; BOS TAURUS BILE 8 [hp_X]/1 mL; PORK LIVER 9 [hp_X]/1 mL; GOLDENSEAL 5 [hp_X]/1 mL; VERONICASTRUM VIRGINICUM ROOT 12 [hp_X]/1 mL; MAGNESIUM PHOSPHATE, DIBASIC TRIHYDRATE 12 [hp_X]/1 mL; SODIUM PHOSPHATE, DIBASIC, HEPTAHYDRATE 6 [hp_X]/1 mL; PODOPHYLLUM 12 [hp_X]/1 mL; TARAXACUM OFFICINALE 4 [hp_X]/1 mL
INACTIVE INGREDIENTS: WATER; ALCOHOL; GLYCERIN

Drug Facts:

ACTIVE INGREDIENTS:

59.1 mL contains 12.5% of Boldo 4X; Carduus Marianus 4X; Echinacea 4X; Hepar Suis 6C; Hydrastis Canadensis 5X; Natrum Phosphoricum 6X; Taraxacum Officinale 4X; 0.83% of: Ammi Visnaga 12X; Atropinum Sulphuricum 12X; Boldo 12X; Chelidonium Majus 12X; Fel Tauri 8X, 12X, 30X; Hepar Suis 9X, 12X, 30X; Leptandra Virginica 12X; Magnesia Phosphorica 12X, 30X; Natrum Phosphoricum 12X; Podophyllum Peltatum 12X.

PURPOSE:

Temporary relief of abdominal discomfort, indigestion, headaches.

WARNINGS:

In case of overdose, get medical help or contact a Poison Control Center right away.

If pregnant or breast feeding, ask a health professional before use.

Keep out of reach of children.

Other information

Store at room temperature out of direct sunlight.

Do not use if neck wrap is broken or missing.

Keep out of reach of children. In case of overdose, get medical help or contact a Poison Control Center right away.

DIRECTIONS:

Take 30 drops orally twice daily or as directed by a healthcare professional.

Consult a physician for use in children under 12 years of age or if symptoms worsen or persist.

USES:

Temporary relief of abdominal discomfort, indigestion, headaches.

INACTIVE INGREDIENTS:

Ethyl Alcohol, Glycerin, Purified Water

QUESTIONS:

Distributed by

Energetix Corp.

Dahlonega, GA 30533

Questions? 800.990.7085

www.goenergetix.com

PACKAGE LABEL DISPLAY:

energetix
GB-Tone
Homeopathic Remedy
Abdominal discomfort, indigestion, headaches.
2 fl oz (59.1 mL)